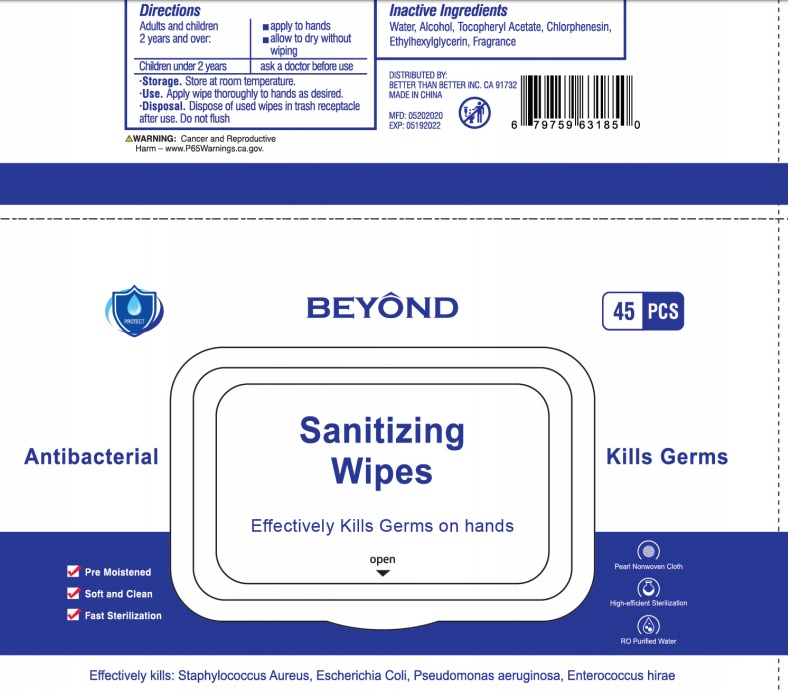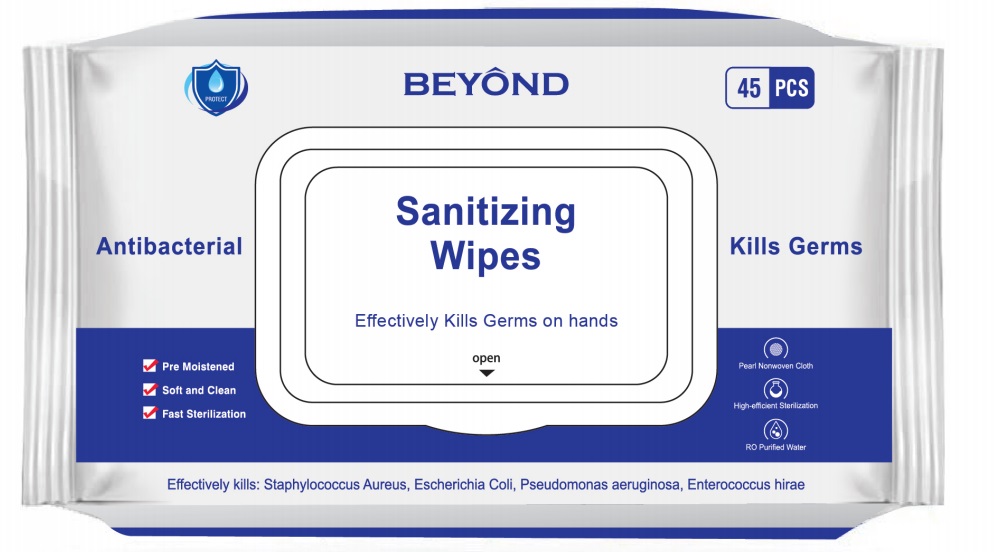 DRUG LABEL: Hand Sanitizing Wipes
NDC: 74168-004 | Form: CLOTH
Manufacturer: Zhejiang Yasili Cosmetics Co., Ltd.
Category: otc | Type: HUMAN OTC DRUG LABEL
Date: 20220308

ACTIVE INGREDIENTS: ALCOHOL 0.33 g/1 1; BENZALKONIUM CHLORIDE 4.888 mg/1 1
INACTIVE INGREDIENTS: WATER; .ALPHA.-TOCOPHEROL ACETATE; CHLORPHENESIN; ETHYLHEXYLGLYCERIN

Hand Sanitizing Wipes

Active Ingredient

Benzalkonium Chloride 0.13%

Purpose

Antimicrobial

Uses

For hand washing to decrease bacteria on the skin

Warnings

For external use only

Do not use if you are allergic to any of the ingredients

When using this product do not get into eyes. If contact occurs, rinse thoroughly with water.

Stop use and ask a doctor if irritation or rash develops and continues for more than 72 hours

Keep out of reach of children. If swallowed, get medical help or contact a Poison Control Center right away.

Directions

Adults and children 2 years and over:

- apply to hands
- allow to dry without wiping

Children under 2 years ask a doctor before use

Inactive Ingredients

water, alcohol, tocopheryl acetate, chlorphenesin, ethylhexylglycerin, fragrance

Beyond Sanitizing Wipes

Antibacterial

Kills Germs

Effectively kills germs on hands

Pre moistened

Soft and clean

Fast sterilization

Pearl nonwoven cloth

High-efficient sterilization

RO purified water

Effectively kills: staphylococcus aureus, escherichia coli, pesudomonas aeruginosa, enterococcus hirae

Storage

- Storage. Store at room temperature.
- Use. Apply wipe thoroughly to hands as desired.
- Disposal. Dispose of used wipes in trash receptacle after use. Do not flush.

Distributed by: Better than Better Inc. CA 91732

Made in China

Warning: Cancer and Reproductive Harm - www.p65warnings.ca.gov.